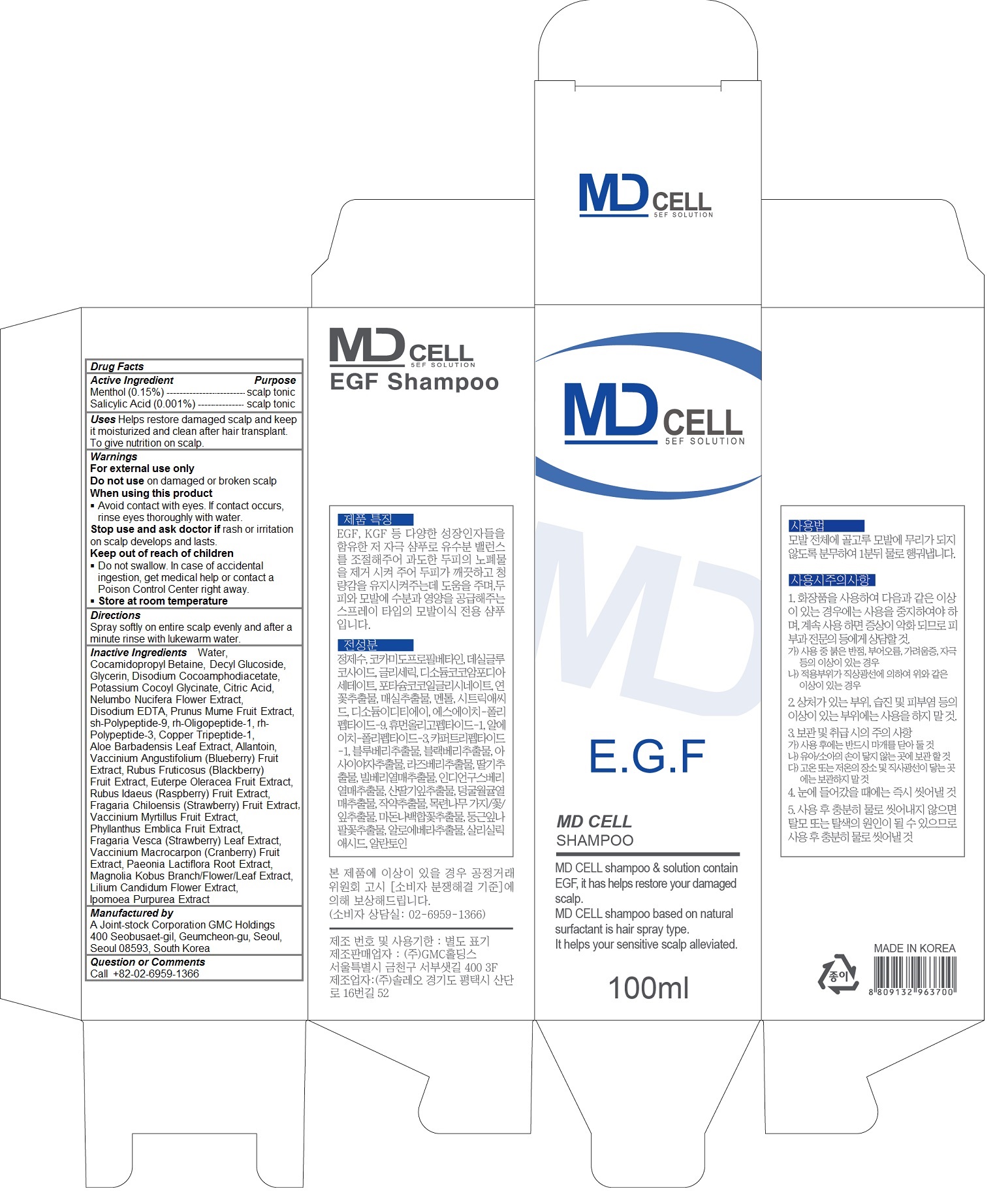 DRUG LABEL: MD CELL
NDC: 70834-103 | Form: SHAMPOO
Manufacturer: A Joint-stock Corporation GMC Holdings
Category: otc | Type: HUMAN OTC DRUG LABEL
Date: 20160722

ACTIVE INGREDIENTS: Menthol 0.0015 1/100 mL; Salicylic Acid 0.00001 1/100 mL
INACTIVE INGREDIENTS: water; Cocamidopropyl Betaine; Decyl Glucoside; Glycerin; Disodium Cocoamphodiacetate; Potassium Cocoyl Glycinate; CITRIC ACID MONOHYDRATE; NELUMBO NUCIFERA FLOWER; EDETATE DISODIUM; PRUNUS MUME FRUIT; NEPIDERMIN; FIBROBLAST GROWTH FACTOR 7; PREZATIDE COPPER; ALOE VERA LEAF; Allantoin; LOWBUSH BLUEBERRY; BLACKBERRY; ACAI; RASPBERRY; BEACH STRAWBERRY; BILBERRY; PHYLLANTHUS EMBLICA FRUIT; FRAGARIA VESCA LEAF; CRANBERRY; PAEONIA LACTIFLORA ROOT; MAGNOLIA KOBUS FLOWERING TOP; LILIUM CANDIDUM FLOWER; IPOMOEA PURPUREA TOP

MD CELL Shampoo

Active Ingredients

Menthol (0.15%)

Salicylic Acid (0.001%)

Purpose

scalp tonic

Uses

Helps restore damaged scalp and keep it moisturized and clean after hair transplant. To give nutrition on scalp.

Keep out of reach of children

Do not swallow. In case of accidental ingestion, get medical help or contact a Poison Control Center right away.

Warnings

For external use only

Do not use on damaged or broken scalp

When using this product
Avoid contact with eyes. If contact occurs, rinse eyes thoroughly with water.

Stop use and ask doctor if rash or irritation on scalp develops and lasts.

Store at room temperature

Directions

Spray softly on entire scalp evenly and after a minute rinse with lukewarm water.

Inactive Ingrediencts

Water, Cocamidopropyl Betaine, Decyl Glucoside, Glycerin, Disodium Cocoamphodiacetate, Potassium Cocoyl Glycinate, Citric Acid, Nelumbo Nucifera Flower Extract, Disodium EDTA, Prunus Mume Fruit Extract, sh-Polypeptide-9, rh-Oligopeptide-1, rh-Polypeptide-3, Copper Tripeptide-1, Aloe Barbadensis Leaf Extract, Allantoin, Vaccinium Angustifolium (Blueberry) Fruit Extract, Rubus Fruticosus (Blackberry) Fruit Extract, Euterpe Oleracea Fruit Extract, Rubus Idaeus (Raspberry) Fruit Extract, Fragaria Chiloensis (Strawberry) Fruit Extract, Vaccinium Myrtillus Fruit Extract, Phyllanthus Emblica Fruit Extract, Fragaria Vesca (Strawberry) Leaf Extract, Vaccinium Macrocarpon (Cranberry) Fruit Extract, Paeonia Lactiflora Root Extract, Magnolia Kobus Branch/Flower/Leaf Extract, Lilium Candidum Flower Extract, Ipomoea Purpurea Extract